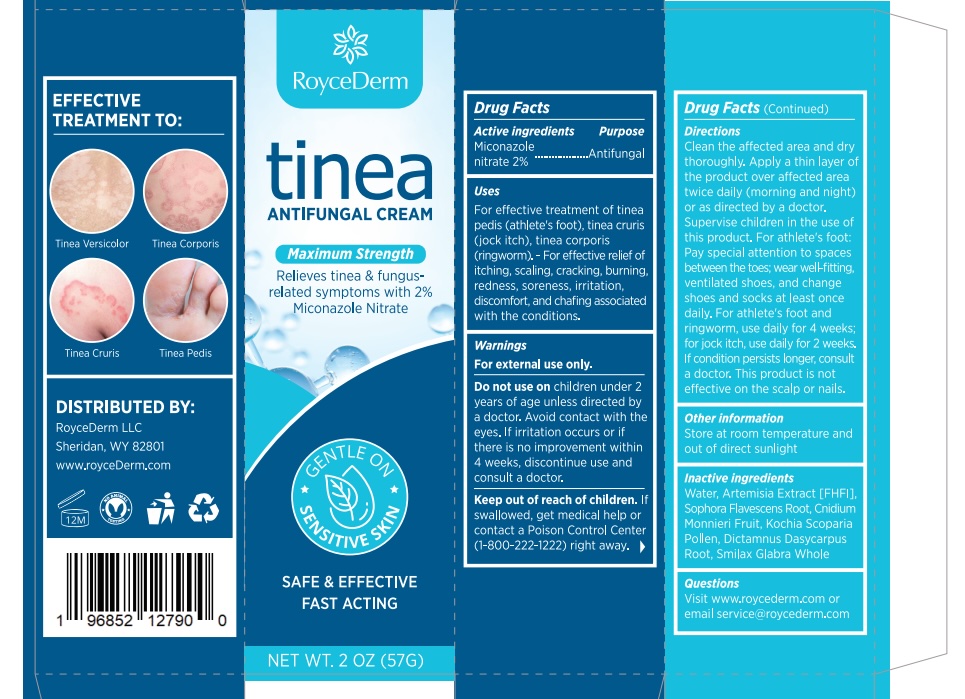 DRUG LABEL: RoyceDerm Tinea Antifungal Cream
NDC: 85424-011 | Form: CREAM
Manufacturer: RoyceDerm LLC
Category: otc | Type: HUMAN OTC DRUG LABEL
Date: 20250930

ACTIVE INGREDIENTS: MICONAZOLE NITRATE 20 mg/1 g
INACTIVE INGREDIENTS: CNIDIUM MONNIERI FRUIT; WORMWOOD; SOPHORA FLAVESCENS ROOT; SMILAX GLABRA WHOLE; BASSIA SCOPARIA POLLEN; DICTAMNUS DASYCARPUS ROOT; WATER

Initial Drug Listing - RoyceDerm Tinea Antifungal Cream

ACTIVE INGREDIENT

Miconazole Nitrate 2%

PURPOSE

Antifungal

INDICATIONS AND USAGE

- For effective treatment of tinea pedis (athlete's foot), tinea cruris (jock itch), tinea corporis (ringworm).

- For effective relief of itching, scaling, cracking, burning, redness, soreness, irritation, discomfort, and chafing associated with the conditions.

WARNINGS

For external use only

Do not use on children under 2 years of age unless directed by a doctor.

WHEN USING

Avoid contact with the eyes.

STOP USE

If irritation occurs or if there is no improvement within 4 weeks, discountine use and consult a doctor.

Keep out of reach of children. If swallowed, get medical help or contact a Poison Control Center (1-800-222-1222) right away.

DOSAGE AND ADMINISTRATION

Clean the affected area and dry thoroughly.

Apply a thin layer of the product over affected area twice daily (morning and night) or as directed by a doctor.

Supervise children in the use of this product.

For athlete’s foot: Pay special attention to spaces between the toes; wear well-fitting, ventilated shoes, and change shoes and socks at least once daily.

For athlete’s foot and ringworm, use daily for 4 weeks; for jock itch, use daily for 2 weeks. If condition persists longer, consult a doctor.

This product is not effective on the scalp or nails.

OTHER SAFETY INFORMATION

Store at room temperature and out of direct sunlight.

INACTIVE INGREDIENT

WATER, ARTEMISIA EXTRACT IFHFI], SOPHORA FLAVESCENS ROOT. CNIDIUM MONNIERI FRUITKOCHIA SCOPARIA POLLEN
DICTAMNUS DASYCARPUSROOT, SMILAX GLABRA WHOLE

QUESTIONS

Visit www.roycederm.com or email service@roycederm.com